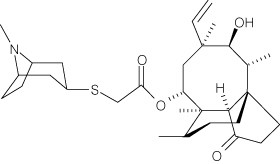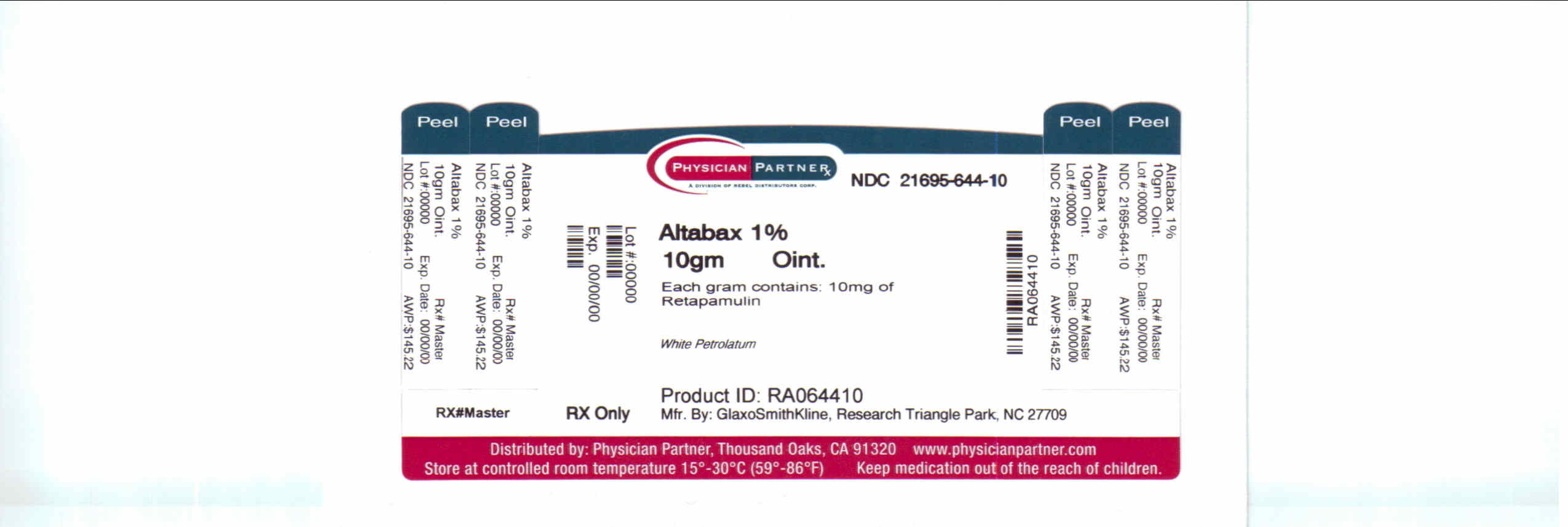 DRUG LABEL: Altabax
NDC: 21695-644 | Form: OINTMENT
Manufacturer: Rebel Distributors Corp.
Category: prescription | Type: HUMAN PRESCRIPTION DRUG LABEL
Date: 20100902

ACTIVE INGREDIENTS: RETAPAMULIN 10 mg/1 g
INACTIVE INGREDIENTS: PETROLATUM

FULL PRESCRIBING INFORMATION

1 INDICATIONS AND USAGE

ALTABAX is indicated for use in adults and pediatric patients aged 9 months and older for the topical treatment of impetigo (up to 100 cm^2 in total area in adults or 2% total body surface area in pediatric patients aged 9 months or older) due to Staphylococcus aureus (methicillin-susceptible isolates only) or Streptococcus pyogenes [see Clinical Studies (14)].

To reduce the development of drug-resistant bacteria and maintain the effectiveness of ALTABAX and other antibacterial drugs, ALTABAX should

2 DOSAGE AND ADMINISTRATION

A thin layer of ALTABAX should be applied to the affected area (up to 100 cm^2 in total area in adults or 2% total body surface area in pediatric patients aged 9 months or older) twice daily for 5 days. The treated area may be covered with a sterile bandage or gauze dressing if desired [see Patient Counseling Information (17)].

3 DOSAGE FORMS AND STRENGTHS

10 mg retapamulin/1g of ointment in 5, 10, 15, and 30 gram tubes

4 CONTRAINDICATIONS

None.

5 WARNINGS AND PRECAUTIONS

5.1 Local Irritation

In the event of sensitization or severe local irritation from ALTABAX, usage should be discontinued, the ointment wiped off, and appropriate alternative therapy for the infection instituted [see Patient Counseling Information (17)].

5.2 Not for Systemic or Mucosal Use

ALTABAX is not intended for ingestion or for oral, intranasal, ophthalmic, or intravaginal use. ALTABAX has not been evaluated for use on mucosal surfaces [see Patient Counseling Information (17)].

5.3 Potential for Microbial Overgrowth

The use of antibiotics may promote the selection of nonsusceptible organisms. Should superinfection occur during therapy, appropriate measures should be taken.

Prescribing ALTABAX in the absence of a proven or strongly suspected bacterial infection is unlikely to provide benefit to the patient and increases the risk of the development of drug-resistant bacteria.

6 ADVERSE REACTIONS

6.1 Clinical Studies Experience

The safety profile of ALTABAX was assessed in 2,115 adult and pediatric patients ≥9 months who used at least one dose from a 5-day, twice a day regimen of retapamulin ointment. Control groups included 819 adult and pediatric patients who used at least one dose of the active control (oral cephalexin), 172 patients who used an active topical comparator (not available in the US), and 71 patients who used placebo.

Adverse events rated by investigators as drug-related occurred in 5.5% (116/2,115) of patients treated with retapamulin ointment, 6.6% (54/819) of patients receiving cephalexin, and 2.8% (2/71) of patients receiving placebo. The most common drug-related adverse events (≥1% of patients) were application site irritation (1.4%) in the retapamulin group, diarrhea (1.7%) in the cephalexin group, and application site pruritus (1.4%) and application site paresthesia (1.4%) in the placebo group.

Because clinical studies are conducted under varying conditions, adverse reaction rates observed in the clinical studies of a drug cannot be directly compared to rates in the clinical studies of another drug and may not reflect the rates observed in practice. The adverse reaction information from the clinical studies does, however, provide a basis for identifying the adverse events that appear to be related to drug use and for approximating rates.

Adults

The adverse events, regardless of attribution, reported in at least 1% of adults (18 years of age and older) who received ALTABAX are listed in Table 1.

Table 1. Adverse Events Reported by Greater Than or Equal To 1% of Adult Patients Treated With ALTABAX in Phase 3 Clinical Studies
Adverse Event | ALTABAX; N = 1,527; % | Cephalexin; N = 698; %
Headache | 2.0 | 2.0
Application site irritation | 1.6 | Less than 1.0
Diarrhea | 1.4 | 2.3
Nausea | 1.2 | 1.9
Nasopharyngitis | 1.2 | Less than 1.0
Creatinine phosphokinase increased | Less than 1.0 | 1.0

Pediatrics

The adverse events, regardless of attribution, reported in at least 1% of pediatric patients aged 9 months to 17 years who received ALTABAX are listed in Table 2.

Table 2. Adverse Events Reported by Greater Than or Equal To 1% in Pediatric Patients Aged 9 Months to 17 Years Treated With ALTABAX in Phase 3 Clinical Studies
Adverse Event | ALTABAX; N = 588; % | Cephalexin; N = 121; % | Placebo; N = 64; %
Application site pruritus | 1.9 | 0 | 0
Diarrhea | 1.7 | 5.0 | 0
Nasopharyngitis | 1.5 | 1.7 | 0
Pruritus | 1.5 | 1.0 | 1.6
Eczema | 1.0 | 0 | 0
Headache | 1.2 | 1.7 | 0
Pyrexia | 1.2 | Less than 1.0 | 1.6

Other Adverse Events

Application site pain, erythema, and contact dermatitis were reported in less than 1% of patients in clinical studies.

7 DRUG INTERACTIONS

Co-administration of oral ketoconazole 200 mg twice daily increased retapamulin geometric mean AUC(0-24) and Cmax by 81% after topical application of retapamulin ointment, 1% on the abraded skin of healthy adult males. Due to low systemic exposure to retapamulin following topical application in patients, dosage adjustments for retapamulin are unnecessary when co-administered with CYP3A4 inhibitors, such as ketoconazole. Based on in vitro P450 inhibition studies and the low systemic exposure observed following topical application of ALTABAX, retapamulin is unlikely to affect the metabolism of other P450 substrates.

The effect of concurrent application of ALTABAX and other topical products to the same area of skin has not been studied.

8 USE IN SPECIFIC POPULATIONS

8.1 Pregnancy

Pregnancy Category B. Effects on embryo-fetal development were assessed in pregnant rats given 50, 150, or 450 mg/kg/day by oral gavage on days 6 to 17 postcoitus. Maternal toxicity (decreased body weight gain and food consumption) and developmental toxicity (decreased fetal body weight and delayed skeletal ossification) were evident at doses ≥150 mg/kg/day. There were no treatment-related malformations observed in fetal rats.

Retapamulin was given as a continuous intravenous infusion to pregnant rabbits at dosages of 2.4, 7.2, or 24 mg/kg/day from day 7 to 19 of gestation. Maternal toxicity (decreased body weight gain, food consumption, and abortions) was demonstrated at dosages ≥7.2 mg/kg/day (8-fold the estimated maximum achievable human exposure, based on AUC, at 7.2 mg/kg/day). There was no treatment-related effect on embryo-fetal development.

There are no adequate and well-controlled studies in pregnant women. Because animal reproduction studies are not always predictive of human response, ALTABAX should be used in pregnancy only when the potential benefits outweigh the potential risk.

8.3 Nursing Mothers

It is not known whether retapamulin is excreted in human milk. Because many drugs are excreted in human milk, caution should be exercised when ALTABAX is administered to a nursing woman. The safe use of retapamulin during breast-feeding has not been established.

8.4 Pediatric Use

The safety and effectiveness of ALTABAX in the treatment of impetigo have been established in pediatric patients 9 months to 17 years of age. Use of ALTABAX in pediatric patients is supported by evidence from adequate and well-controlled studies of ALTABAX in which 588 pediatric patients received at least one dose of retapamulin ointment, 1% [see Adverse Reactions (6), Clinical Studies (14)]. The magnitude of efficacy and the safety profile of ALTABAX in pediatric patients 9 months and older were similar to those in adults.

The safety and effectiveness of ALTABAX in pediatric patients younger than 9 months of age have not been established.

8.5 Geriatric Use

Of the total number of patients in the adequate and well-controlled studies of ALTABAX, 234 patients were 65 years of age and older, of whom 114 patients were 75 years of age and older. No overall differences in effectiveness or safety were observed between these patients and younger adult patients.

10 OVERDOSAGE

Overdosage with ALTABAX has not been reported. Any signs or symptoms of overdose, either topically or by accidental ingestion, should be treated symptomatically consistent with good clinical practice.

There is no known antidote for overdoses of ALTABAX.

11 DESCRIPTION

ALTABAX contains retapamulin, a semisynthetic pleuromutilin antibiotic. The chemical name of retapamulin is acetic acid, [[(3-exo)-8-methyl-8-azabicyclo[3.2.1]oct-3-yl]thio]-, (3aS,4R,5S,6S,8R,9R,9aR,10R)-6-ethenyldecahydro-5-hydroxy-4,6,9,10-tetramethyl-1-oxo-3a,9-propano-3aH-cyclopentacycloocten-8-yl ester. Retapamulin, a white to pale-yellow crystalline solid, has a molecular formula of C30H47NO4S, and a molecular weight of 517.78. The chemical structure is:

Each gram of ointment for dermatological use contains 10 mg of retapamulin in white petrolatum.

12 CLINICAL PHARMACOLOGY

12.1 Mechanism of Action

ALTABAX is an antibacterial agent [see Clinical Pharmacology (12.4)].

12.2 Pharmacodynamics

In post-hoc analyses of manually over-read 12-lead ECGs from healthy subjects (N = 103), no significant effects on QT/QTc intervals were observed after topical application of retapamulin ointment on intact and abraded skin. Due to the low systemic exposure to retapamulin with topical application, QT prolongation in patients is unlikely [see Clinical Pharmacology (12.3)].

12.3 Pharmacokinetics

Absorption

In a study of healthy adult subjects, retapamulin ointment, 1% was applied once daily to intact skin (800 cm^2 surface area) and to abraded skin (200 cm^2 surface area) under occlusion for up to 7 days. Systemic exposure following topical application of retapamulin through intact and abraded skin was low. Three percent of blood samples obtained on Day 1 after topical application to intact skin had measurable retapamulin concentrations (lower limit of quantitation 0.5 ng/mL); thus Cmax values on Day 1 could not be determined. Eighty-two percent of blood samples obtained on Day 7 after topical application to intact skin and 97% and 100% of blood samples obtained after topical application to abraded skin on Days 1 and 7, respectively, had measurable retapamulin concentrations. The median Cmax value in plasma after application to 800 cm^2 of intact skin was 3.5 ng/mL on Day 7 (range 1.2 to 7.8 ng/mL). The median Cmax value in plasma after application to 200 cm^2 of abraded skin was 11.7 ng/mL on Day 1 (range 5.6 to 22.1 ng/mL) and 9.0 ng/mL on Day 7 (range 6.7 to 12.8 ng/mL).

Plasma samples were obtained from 380 adult patients and 136 pediatric patients (aged 2-17 years) who were receiving topical treatment with ALTABAX topically twice daily. Eleven percent had measurable retapamulin concentrations (lower limit of quantitation 0.5 ng/mL), of which the median concentration was 0.8 ng/mL. The maximum measured retapamulin concentration in adults was 10.7 ng/mL and in pediatric patients was 18.5 ng/mL.

Distribution

Retapamulin is approximately 94% bound to human plasma proteins, and the protein binding is independent of concentration. The apparent volume of distribution of retapamulin has not been determined in humans.

Metabolism

In vitro studies with human hepatocytes showed that the main routes of metabolism were mono-oxygenation and di-oxygenation. In vitro studies with human liver microsomes demonstrated that retapamulin is extensively metabolized to numerous metabolites, of which the predominant routes of metabolism were mono-oxygenation and N-demethylation. The major enzyme responsible for metabolism of retapamulin in human liver microsomes was cytochrome P450 3A4 (CYP3A4).

Elimination

Retapamulin elimination in humans has not been investigated due to low systemic exposure after topical application.

12.4 Microbiology

Retapamulin is a semisynthetic derivative of the compound pleuromutilin, which is isolated through fermentation from Clitopilus passeckerianus (formerly Pleurotus passeckerianus). In vitro activity of retapamulin against isolates of Staphylococcus aureus as well as Streptococcus pyogenes has been demonstrated.

Antimicrobial Mechanism of Action

Retapamulin selectively inhibits bacterial protein synthesis by interacting at a site on the 50S subunit of the bacterial ribosome through an interaction that is different from that of other antibiotics. This binding site involves ribosomal protein L3 and is in the region of the ribosomal P site and peptidyl transferase center. By virtue of binding to this site, pleuromutilins inhibit peptidyl transfer, block P-site interactions, and prevent the normal formation of active 50S ribosomal subunits. Retapamulin is bacteriostatic against Staphylococcus aureus and Streptococcus pyogenes at the retapamulin in vitro minimum inhibitory concentration (MIC) for these organisms. At concentrations 1,000x the in vitro MIC, retapamulin is bactericidal against these same organisms. Retapamulin demonstrates no in vitrotarget-specific cross-resistance with other classes of antibiotics.

Mechanisms of Decreased Susceptibility to Retapamulin

In vitro, 2 mechanisms that cause reduced susceptibility to retapamulin have been identified, specifically, mutations in ribosomal protein L3 or the presence of an efflux mechanism. Decreased susceptibility of S. aureus to retapamulin (highest retapamulin MIC was 2 mcg/mL) develops slowly in vitro via multistep mutations in L3 after serial passage in sub-inhibitory concentrations of retapamulin. There was no apparent treatment-associated reduction in susceptibility to retapamulin in the Phase 3 clinical program. The clinical significance of these findings is not known.

Other

Based on in vitro broth microdilution susceptibility testing, no differences were observed in susceptibility of S. aureus to retapamulin whether the isolates were methicillin-resistant or methicillin-susceptible. Retapamulin susceptibility did not correlate with clinical success rates in patients with methicillin-resistant S.aureus. The reason for this is not known but may have been influenced by the presence of particular strains of S. aureus possessing certain virulence factors, such as Panton-Valentine Leukocidin (PVL). In the case of treatment failure associated with S. aureus (regardless of methicillin susceptibility), the presence of strains possessing additional virulence factors (such as PVL) should be considered.

Retapamulin has been shown to be active against the following microorganisms, both in vitro and in clinical trials [see Indications and Usage (1)].

Aerobic and Facultative Gram-Positive Bacteria

Staphylococcus aureus (methicillin-susceptible isolates only)

Streptococcus pyogenes

Susceptibility Testing

The clinical microbiology laboratory should provide cumulative results of the in vitro susceptibility test results for antimicrobial drugs used in local hospitals and practice areas to the physician as periodic reports that describe the susceptibility profile of nosocomial and community-acquired pathogens. These reports should aid the physician in selecting the most effective antimicrobial.

Susceptibility Testing Techniques

Dilution Techniques

Quantitative methods can be used to determine the minimum inhibitory concentration (MIC) of retapamulin that will inhibit the growth of the bacteria being tested. The MIC provides an estimate of the susceptibility of bacteria to retapamulin. The MIC should be determined using a standardized procedure.^1,2 Standardized procedures are based on a dilution method (broth or agar) or equivalent with standardized inoculum concentrations and standardized concentrations of retapamulin powder.

Diffusion Techniques

Quantitative methods that require measurement of zone diameters also provide reproducible estimates of the susceptibility of bacteria to antimicrobial compounds. One such standardized procedure requires the use of standardized inoculum concentrations.^2,3 This procedure uses paper disks impregnated with 2 mcg of retapamulin to test the susceptibility of microorganisms to retapamulin.

Susceptibility Test Interpretive Criteria

In vitro susceptibility test interpretive criteria for retapamulin have not been determined for this topical antimicrobial. The relation of the in vitro MIC and/or disk diffusion susceptibility test results to clinical efficacy of retapamulin against the bacteria tested should be monitored.

Quality Control Parameters for Susceptibility Testing

In vitro susceptibility test quality control parameters were developed for retapamulin so that laboratories that test the susceptibility of bacterial isolates to retapamulin can determine if the susceptibility test is performing correctly. Standardized dilution techniques and diffusion methods require the use of laboratory control microorganisms to monitor the technical aspects of the laboratory procedures. Standard retapamulin powder should provide the following MIC and a 2 mcg retapamulin disk should produce the following zone diameters with the indicated quality control strains in Table 3.

Table 3. Acceptable Quality Control Ranges for Retapamulin
Microorganism | MIC Range (mcg/mL) | Disk Diffusion Zone Diameter (mm)
Staphylococcus aureus ATCC 29213 | 0.06-0.25 | NA
Staphylococcus aureus ATCC 25923 | NA | 23-30
Streptococcus pneumoniae ATCC 49619 | 0.06-0.5a | 13-19b

NA = Not applicable.

a This quality control range is applicable using cation-adjusted Mueller-Hinton broth with 2-5% lysed horse blood.

b This quality control limit is applicable using Mueller-Hinton agar with 5% sheep blood.

13 NONCLINICAL TOXICOLOGY

13.1 Carcinogenesis, Mutagenesis, Impairment of Fertility

Long-term studies in animals to evaluate carcinogenic potential have not been conducted with retapamulin.

Retapamulin showed no genotoxicity when evaluated in vitro for gene mutation and/or chromosomal effects in the mouse lymphoma cell assay, in cultured human peripheral blood lymphocytes, or when evaluated in vivo in a rat micronucleus test.

No evidence of impaired fertility was found in male or female rats given retapamulin 50, 150, or 450 mg/kg/day orally.

14 CLINICAL STUDIES

ALTABAX was evaluated in a placebo-controlled study that enrolled adult and pediatric patients 9 months of age and older for treatment of impetigo up to 100 cm^2 in total area (up to 10 lesions) or a total body surface area not exceeding 2%. The majority of patients enrolled (164/210, 78%) were under the age of 13. The study was a double-blind, randomized, multi-center, parallel-group comparison of the safety of ALTABAX and placebo ointment, both applied twice daily for 5 days. The study was randomized 2 ALTABAX to 1 placebo patient. Patients with underlying skin disease (e.g., preexisting eczematous dermatitis) or skin trauma, with clinical evidence of secondary infection were excluded from these studies. In addition, patients with any systemic signs and symptoms of infection (such as fever) were excluded from the study. Clinical success was defined as the absence of treated lesions, or treated lesions had become dry without crusts with or without erythema compared to baseline, or had improved (defined as a decline in the size of the affected area, number of lesions or both) such that no further antimicrobial therapy was required. The intent-to-treat clinical (ITTC) population consisted of all randomized patients who took at least 1 dose of study medication. The clinical per protocol (PPC) population included all ITTC patients who satisfied the inclusion/exclusion criteria and subsequently adhered to the protocol. The intent-to-treat bacteriological (ITTB) population consisted of all randomized patients who took at least one dose of study medication and had a pathogen identified at study entry. The bacteriological per protocol (PPB) population included all ITTB patients who satisfied the inclusion/exclusion criteria and subsequently adhered to the protocol.

The following table describes the results for clinical response at end of therapy (2 days after treatment) and follow-up (9 days after treatment), by analysis population:

Table 4. Clinical Response at End of Therapy and at Follow-Up by Analysis Population
Analysis Population | ALTABAX | Placebo | Difference in Success Rates (%) | 95% CI (%)
n/N | Success Rate (%) | n/N | Success Rate (%)
End of Therapy
PPC | 111/124 | 89.5 | 33/62 | 53.2 | 36.3 | (22.8, 49.8)
ITTC | 119/139 | 85.6 | 37/71 | 52.1 | 33.5 | (20.5, 46.5)
PPB | 96/107 | 89.7 | 26/52 | 50.0 | 39.7 | (25.0, 54.5)
ITTB | 101/114 | 88.6 | 28/57 | 49.1 | 39.5 | (25.2, 53.7)
Follow-Up
PPC | 98/119 | 82.4 | 25/58 | 43.1 | 39.2 | (24.8, 53.7)
ITTC | 105/139 | 75.5 | 28/71 | 39.4 | 36.1 | (22.7, 49.5)
PPB | 86/102 | 84.3 | 18/48 | 37.5 | 46.8 | (31.4, 62.2)
ITTB | 91/114 | 79.8 | 19/57 | 33.3 | 46.5 | (32.2, 60.8)

n = number with clinical success outcome, N = number in analysis population, PPC = Clinical Per Protocol Population, ITTC = Clinical Intent to Treat Population, PPB = Bacteriological Per Protocol Population, ITTB = Bacteriological Intent to Treat Population

The following table describes the clinical success at end of therapy and follow-up by baseline pathogen:

Table 5. Clinical Response at End of Therapy and Follow-Up for Patients With Staphylococcus aureus and Streptococcus pyogenes at Baseline in the Per Protocol Bacteriological Population (PPB)
Pathogen | ALTABAX | Placebo
n/N | Success Rate (%) | n/N | Success Rate (%)
End of Therapy
Staphylococcus aureus (Methicillin-susceptible) | 79/88 | 89.8 | 25/48 | 52.1
Streptococcus pyogenes | 29/32 | 90.6 | 3/7 | 42.9
Follow-Up
Staphylococcus aureus (Methicillin-susceptible) | 71/84 | 84.5 | 19/44 | 43.2
Streptococcus pyogenes | 29/32 | 90.6 | 2/6 | 33.3

n/N = number of clinical successes/number of pathogens isolated at baseline.

Examination of age and gender subgroups did not identify differences in response to ALTABAX among these groups. The majority of patients entered into this study were classified as White/Caucasian or of Asian heritage; when response rates by racial subgroups were viewed across studies, differences in response to ALTABAX were not identified.

15 REFERENCES

1. Clinical and Laboratory Standards Institute (CLSI) Methods for Dilution Antimicrobial Susceptibility Tests for Bacteria that Grow Aerobically. Approved Standard. CLSI Document M7-A7. CLSI, Wayne, PA, Jan. 2006.
2. Clinical and Laboratory Standards Institute (CLSI). Performance Standards for Antimicrobial Susceptibility Testing – 17th Informational Standard. M100-S17. CLSI, Wayne, PA, Jan. 2007.
3. Clinical and Laboratory Standards Institute (CLSI). Performance Standards for Antimicrobial Disk Susceptibility Tests. Approved Standard. CLSI Document M2-A9. CLSI, Wayne, PA, Jan. 2006.

16 HOW SUPPLIED/STORAGE AND HANDLING

ALTABAX is supplied in 10 gram tubes.

NDC 21695-644-10 (10 gram tube)

Store at 25°C (77°F) with excursions permitted to 15°-30°C (59°-86°F).

17 PATIENT COUNSELING INFORMATION

Patients using ALTABAX and/or their guardians should receive the following information and instructions: Use ALTABAX as directed by the healthcare practitioner. As with any topical medication, patients and caregivers should wash their hands after application if the hands are not the area for treatment.

- ALTABAX is for external use only. Do not swallow ALTABAX or use it in the eyes, on the mouth or lips, inside the nose, or inside the female genital area.
- The treated area may be covered by a sterile bandage or gauze dressing, if desired. This may also be helpful for infants and young children who accidentally touch or lick the lesion site. A bandage will protect the treated area and avoid accidental transfer of ointment to the eyes or other areas.
- Use the medication for the full time recommended by the healthcare practitioner, even though symptoms may have improved.
- Notify the healthcare practitioner if there is no improvement in symptoms within 3 to 4 days after starting use of ALTABAX.
- ALTABAX may cause reactions at the site of application of the ointment. Inform the healthcare practitioner if the area of application worsens in irritation, redness, itching, burning, swelling, blistering, or oozing.

ALTABAX is a registered trademark of GlaxoSmithKline.

GlaxoSmithKline

Research Triangle Park, NC 27709
©2009, GlaxoSmithKline. All rights reserved.

Repackaged by:

Rebel Distributors Corp.

Thousand Oaks, CA 91320

PRINCIPAL DISPLAY PANEL

ALTABAXTM

(retapamulin ointment), 1%

10 grams (Net Wt.)

Rx only